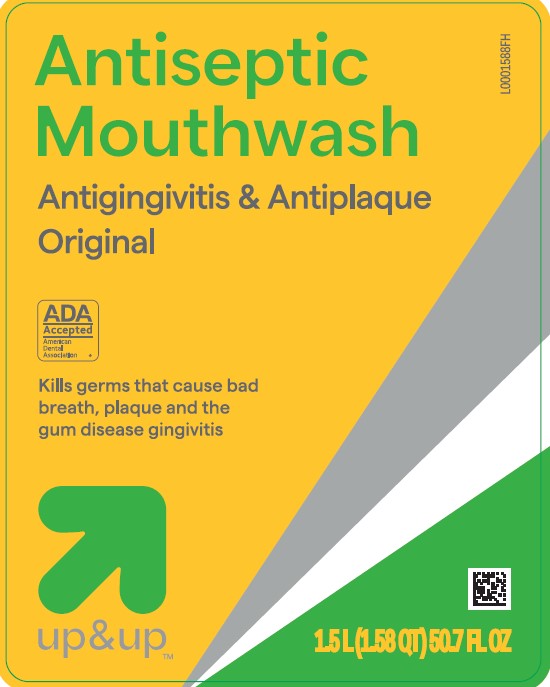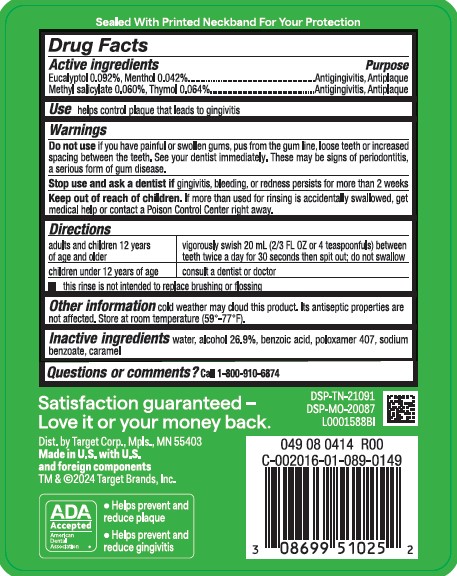 DRUG LABEL: Antiseptic
NDC: 11673-318 | Form: MOUTHWASH
Manufacturer: Target Corporation
Category: otc | Type: HUMAN OTC DRUG LABEL
Date: 20260218

ACTIVE INGREDIENTS: EUCALYPTOL 0.92 mg/1 mL; MENTHOL 0.42 mg/1 mL; METHYL SALICYLATE 0.6 mg/1 mL; THYMOL 0.64 mg/1 mL
INACTIVE INGREDIENTS: WATER; ALCOHOL; BENZOIC ACID; POLOXAMER 407; SODIUM BENZOATE; CARAMEL

Up & Up 318.003/318AH-AI
Antiseptic Mouthrinse

Tamper Evident Statement

Sealed With Printed Neckband For Your Protection

Active ingredients

Eucalyptol 0.092%

Menthol 0.042%

Methyl salicylate 0.060%

Thymol 0.064%

Purpose

Antiginvitis, Antiplaque

Use

helps control plaque that leads to gingivitis

Warnings

for this product

Do not use

if you have painful or swollen gums, pus from the gum line, loose teeth or increased spacing between the teeth. See your dentist immediately. These may be signs of periodontitis, a serious form of gum disease.

Stop use and ask a dentist if

gingivitis, bleeding, or redness persists for more than 2 weeks

Keep out of reach of children.

If more than used for rinsing is accidentally swallowed, get medical help or contact a Poison Control Center right away.

Directions

adults and children 12 years of age and older - vigorously swish 20 mL (2/3 FL OZ or 4 teaspoonfuls) between teeth twice a day for 30 seconds then spit out; do not swallow

children under 12 years of age - consult a dentsit or doctor

- this rinse is not intended to replace brushing or flossing

Other information

cold weather may cloud this product. Its antiseptic properties are not affected. Store at room temperature (59°-77°F).

Inactive ingredients

water, alcohol 26.9%, benzoic acid, poloxamer 407, sodium benzoate, caramel

Adverse reaction section

Satisfaction guaranteed - Love it or your money back.

Dist. by Target Corp., Mpls., MN 55403

Made in U.S. with U.S. and foreign components

TM & ©2024 Target Brands, Inc.

DSP-TN-21091

DSP-MO-20087

ADA Accepted

American Dental Association

- Helps prevent and reduce plaque
- Helps prevent and reduce gingivitis

Principal display panel

Antiseptic Mouthwash

Antigingivitis & Antiplaque

Original

ADA Accepted

American Dental Association

Kills germs that cause bad breath, plaque and the gum disease gingivitis

up & up™

1.5 L (1.58 QT) 50.7 FL OZ